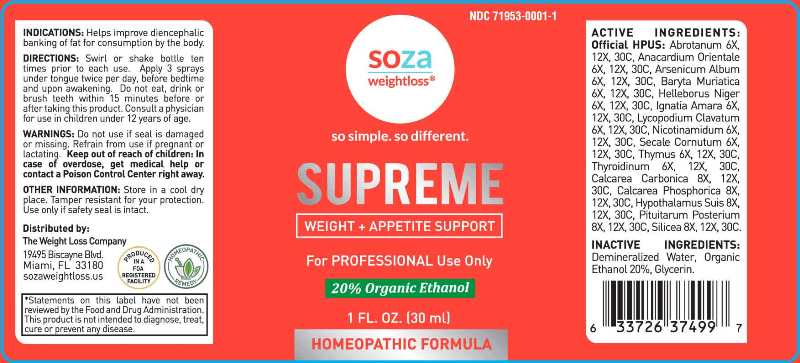 DRUG LABEL: Supreme
NDC: 71953-0001 | Form: LIQUID
Manufacturer: BOUARI GROUP, LLC dba WEIGHT LOSS COMPANY, THE
Category: homeopathic | Type: HUMAN OTC DRUG LABEL
Date: 20200911

ACTIVE INGREDIENTS: ARTEMISIA ABROTANUM FLOWERING TOP 6 [hp_X]/1 mL; ANACARDIUM OCCIDENTALE FRUIT 6 [hp_X]/1 mL; ARSENIC TRIOXIDE 6 [hp_X]/1 mL; BARIUM CHLORIDE DIHYDRATE 6 [hp_X]/1 mL; HELLEBORUS NIGER ROOT 6 [hp_X]/1 mL; STRYCHNOS IGNATII SEED 6 [hp_X]/1 mL; LYCOPODIUM CLAVATUM SPORE 6 [hp_X]/1 mL; NIACINAMIDE 6 [hp_X]/1 mL; CLAVICEPS PURPUREA SCLEROTIUM 6 [hp_X]/1 mL; BOS TAURUS THYMUS 6 [hp_X]/1 mL; THYROID, BOVINE 6 [hp_X]/1 mL; OYSTER SHELL CALCIUM CARBONATE, CRUDE 8 [hp_X]/1 mL; TRIBASIC CALCIUM PHOSPHATE 8 [hp_X]/1 mL; SUS SCROFA HYPOTHALAMUS 8 [hp_X]/1 mL; BOS TAURUS PITUITARY GLAND, POSTERIOR 8 [hp_X]/1 mL; SILICON DIOXIDE 8 [hp_X]/1 mL
INACTIVE INGREDIENTS: WATER; ALCOHOL; GLYCERIN

Drug Facts:

ACTIVE INGREDIENTS:

Abrotanum 6X, 12X, 30C, Anacardium Orientale 6X, 12X, 30C, Arsenicum Album 6X, 12X, 30C, Baryta Muriatica 6X, 12X, 30C, Helleborus Niger 6X, 12X, 30C, Ignatia Amara 6X, 12X, 30C, Lycopodium Clavatum 6X, 12X, 30C, Nicotinamidum 6X, 12X, 30C, Secale Cornutum 6X, 12X, 30C, Thymus (Bovine) 6X, 12X, 30C, Thyroidinum (Bovine) 6X, 12X, 30C, Calcarea Carbonica 8X, 12X, 30C, Calcarea Phosphorica 8X, 12X, 30C, Hypothalamus Suis 8X, 12X, 30C, Pituitarum Posterium (Bovine) 8X, 12X, 30C, Silicea 8X, 12X, 30C.

INDICATIONS:

Helps improve diencephalic banking of fat for consumption by the body.

WARNINGS:

Do not use if seal is damaged or missing.

Refrain from use if pregnant or lactating.

Keep out of reach of children: In case of overdose, get medical help or contact a Poison Control Center right away.

OTHER INFORMATION:

Store in a cool, dry place. Tamper resistant for your protection. Use only if safety seal is intact.

Keep out of reach of children: In case of overdose, get medical help or contact a Poison Control Center right away.

DIRECTIONS:

Swirl or shake bottle ten times prior to each use. Apply 3 sprays under tongue twice per day, before bedtime and upon awakening. Do not eat, drink or brush teeth within 15 minutes before or after taking this product. Consult a physician for use in children under 12 years of age.

INDICATIONS:

Helps improve diencephalic banking of fat for consumption by the body.

INACTIVE INGREDIENTS:

Demineralized Water, Organic Ethanol 20%, Glycerin.

QUESTIONS:

Distributed by:

The Weight Loss Company

19495 Biscayne Blvd.

Miami, FL 33180

sozaweightloss.us

PACKAGE LABEL DISPLAY:

NDC 71953-0001-1

soza

weightloss

so simple. so different.

SUPREME

WEIGHT + APPETITE SUPPORT

For PROFESSIONAL Use Only

1 FL. OZ. (30 ml)

HOMEOPATHIC FORMULA